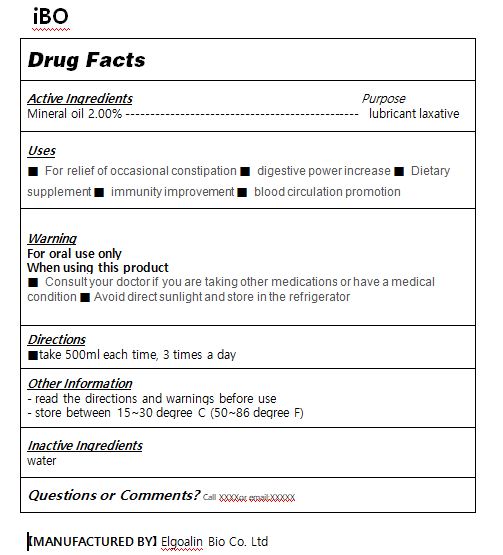 DRUG LABEL: iBO
NDC: 82677-0002 | Form: LIQUID
Manufacturer: Elgoalin Bio Co.,Ltd
Category: otc | Type: HUMAN OTC DRUG LABEL
Date: 20220425

ACTIVE INGREDIENTS: MINERAL OIL 55 g/100 mL
INACTIVE INGREDIENTS: WATER

ACTIVE INGREDIENT

mineral oil

INACTIVE INGREDIENT

water

PURPOSE

For relief of occasional constpation

digestive power increase

Dietary supplement

immunity improvement

blood circulation promotion

keep out of reach of the children

INDICATIONS AND USAGE

Take 500ml each time, 3 times a day

WARNINGS

Consult your doctor if you are taking other medications or have a medical condition
Avoid direct sunlight and store in the refrigerator

DOSAGE AND ADMINISTRATION

for oral use only